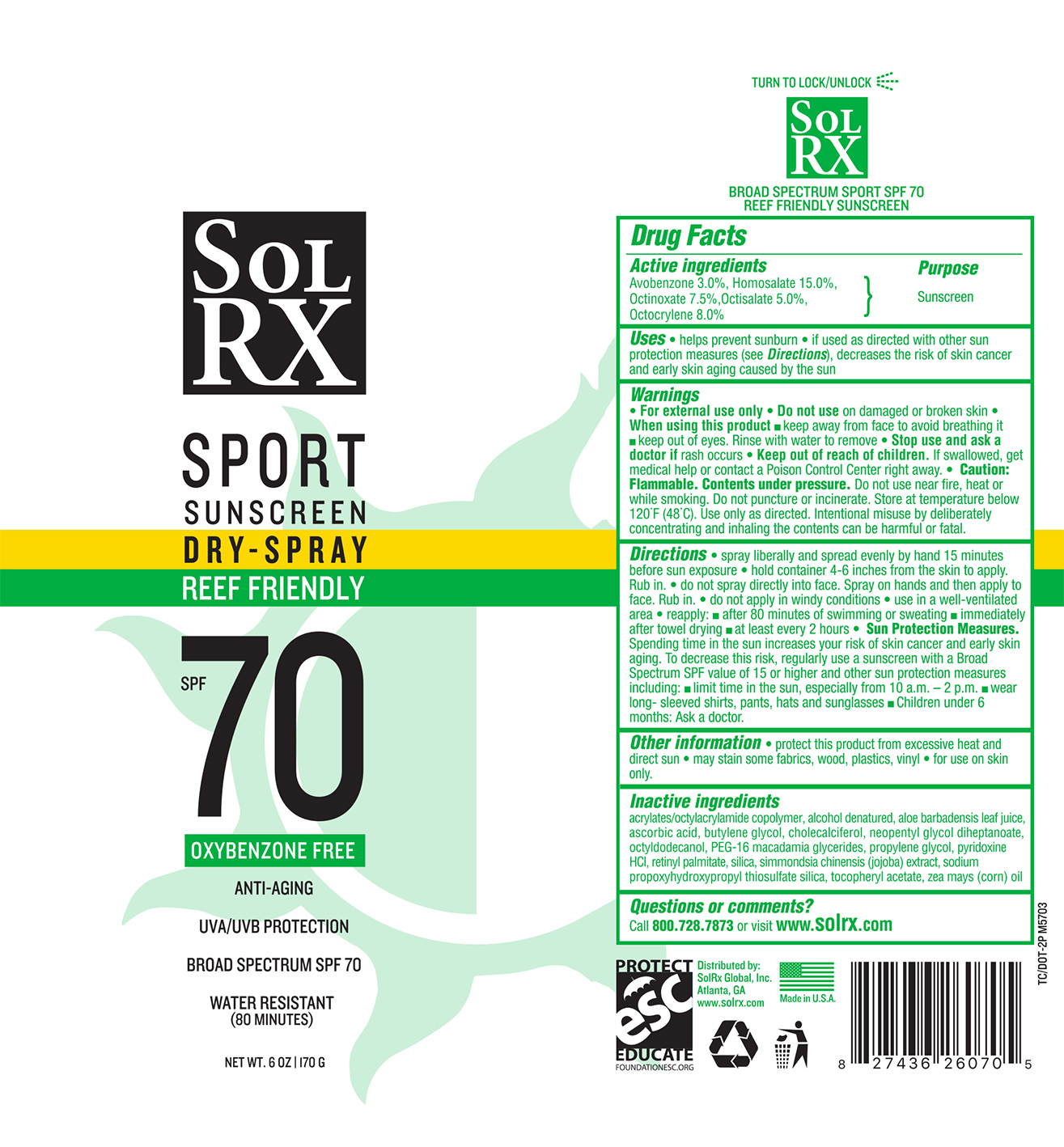 DRUG LABEL: SolRX Sport SPF 70 C-spray
NDC: 73440-6070 | Form: AEROSOL, SPRAY
Manufacturer: Cross Brands Contract Filling
Category: otc | Type: HUMAN OTC DRUG LABEL
Date: 20210219

ACTIVE INGREDIENTS: HOMOSALATE 25.5 g/170 g; OCTINOXATE 12.8 g/170 g; OCTOCRYLENE 13.6 g/170 g; AVOBENZONE 5.1 g/170 g; OCTISALATE 8.5 g/170 g
INACTIVE INGREDIENTS: ALCOHOL 90.4 g/170 g

SolRX Sport SPF 70 C-spray